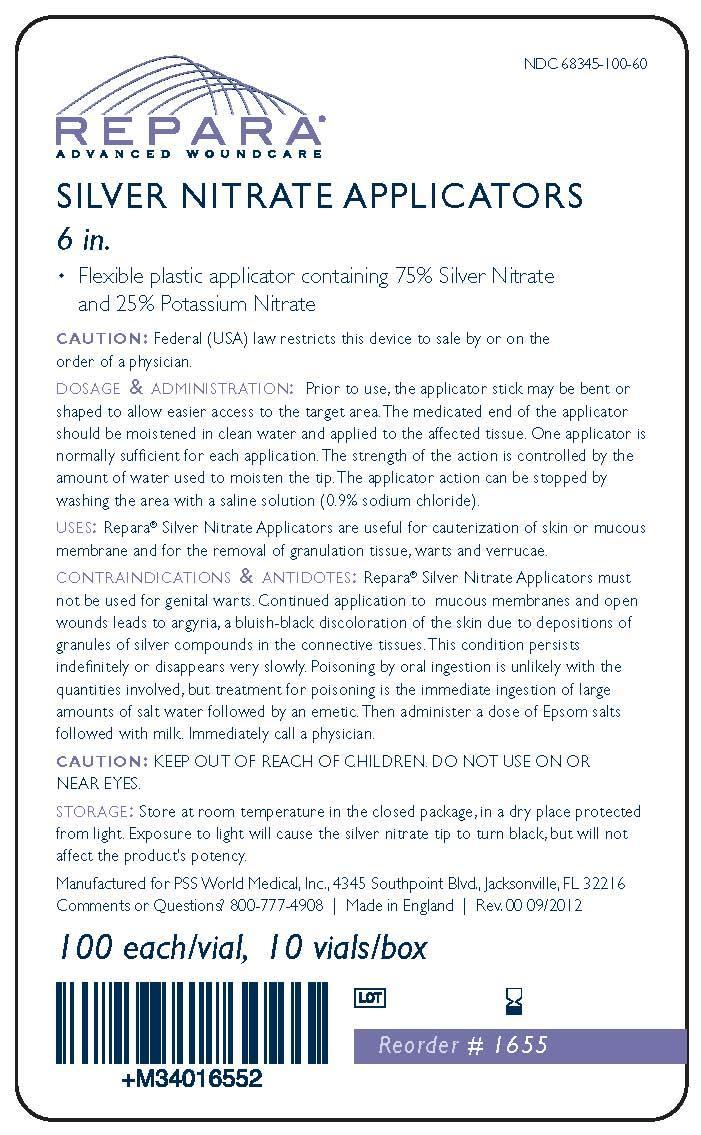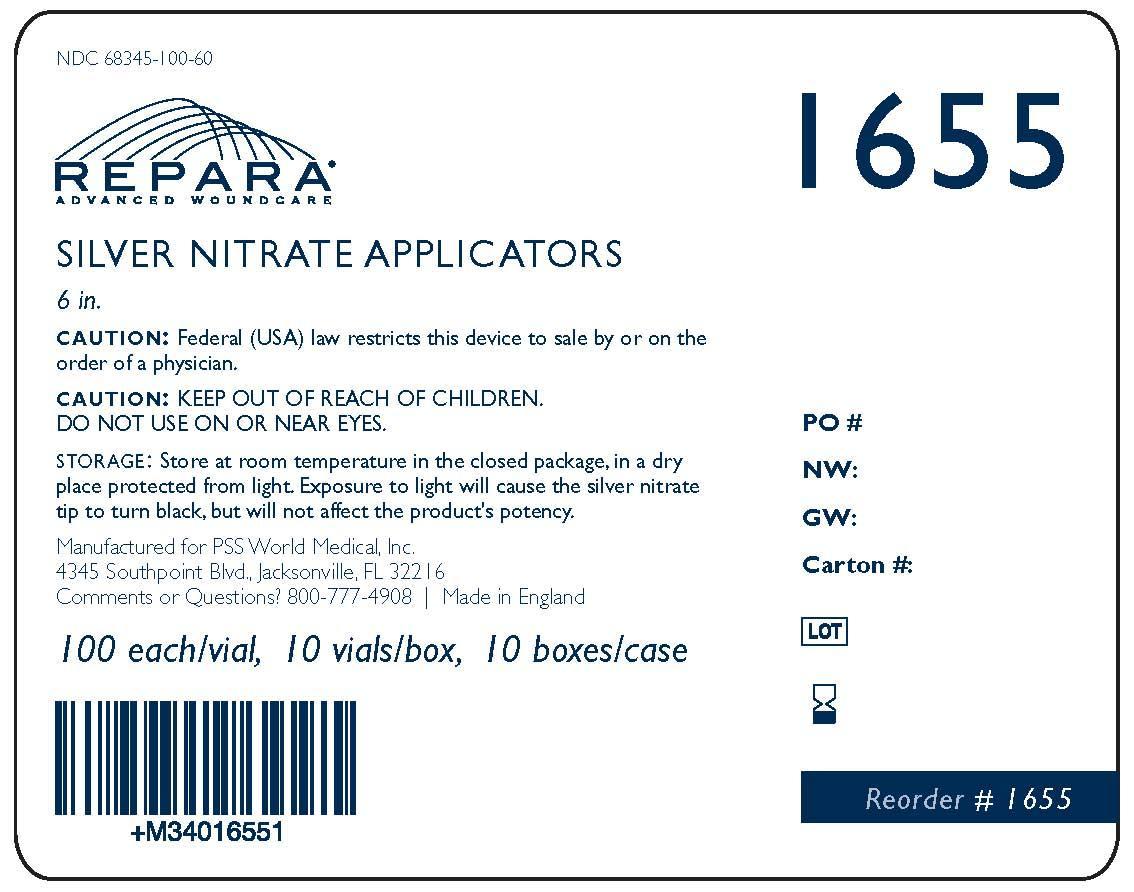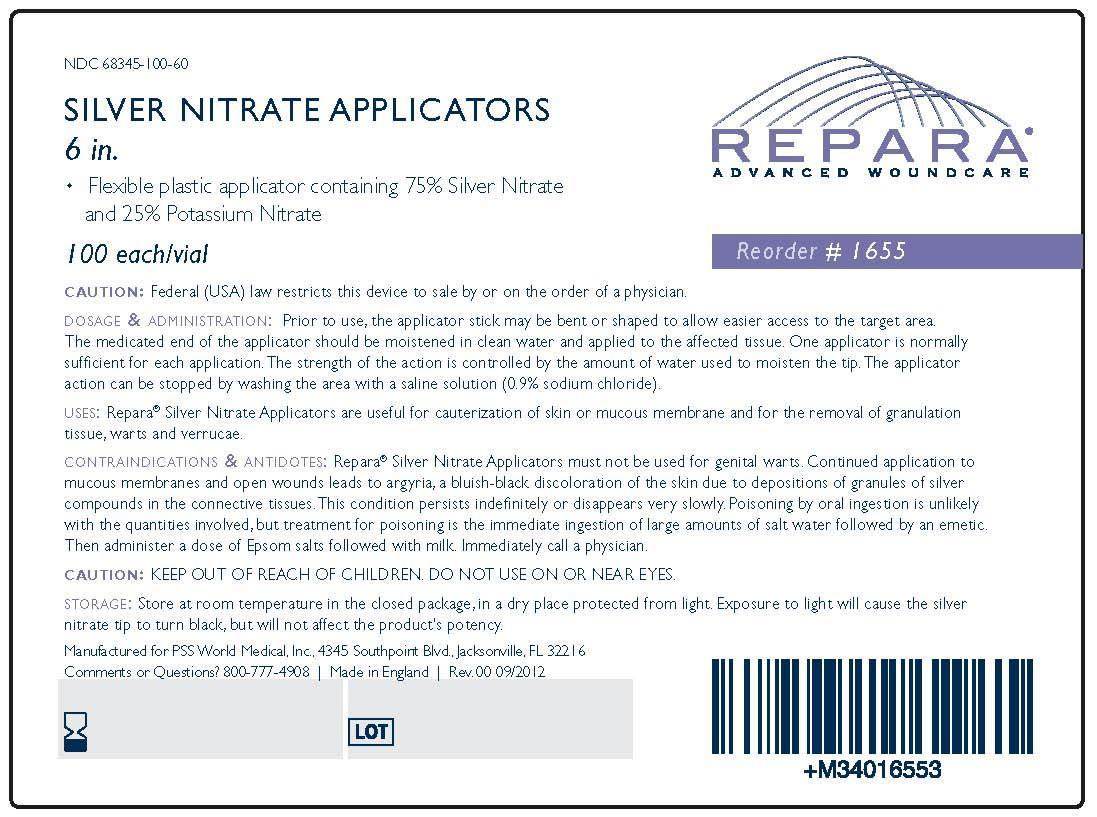 DRUG LABEL: Repara Silver Nitrate
NDC: 68345-100 | Form: STICK
Manufacturer: PSS World Medical, Inc.
Category: prescription | Type: HUMAN PRESCRIPTION DRUG LABEL
Date: 20121026

ACTIVE INGREDIENTS: SILVER NITRATE 75 mg/1 1; POTASSIUM NITRATE 25 mg/1 1

REPARA (Silver Nitrate Applicators)

Active Ingredients

Each flexible plastic applicator contains:

Silver Nitrate.............................75%

Potassium Nitrate.....................25%

CAUTION:

Federal (USA) law restricts this device to sale by or on the order of a physician.

DOSAGE & ADMINISTRATION:

Prior to use, the applicator stick may be bent or shaped to allow easier access to the target area. The medicated end of the applicator should be moistened in clean water and applied to the affected tissue. One applicator is normally sufficient for each application. The strength of the action is controlled by the amount of water used to moisten the tip. The applicator action can be stopped by washing the area with a saline solution (0.9% sodium chloride).

USES:

Repara® Silver Nitrate Applicators are useful for cauterization of skin or mucous membrane and for the removal of granulation tissue, warts and verrucae.

CONTRAINDICATIONS & ANTIDOTES:

Repara® Silver Nitrate Applicators must not be used for genital warts. Continued application to mucous membranes and open wounds leads to argyria, a blush-black discoloration of the skin due to depositions of granules of silver compounds in the connective tissues. This condition persists indefinitely or disappears very slowly. Poisoning by oral ingestion is unlikely with the quantities involved, but treatment for poisoning is the immediate ingestion of large amounts of salt water followed by an emetic. Then administer a dose of Epsom salts followed with milk. Immediately call a physician.

CAUTION:

KEEP OUT OF REACH OF CHILDREN. DO NOT USE ON OR NEAR EYES.

STORAGE:

Store at room temperature in the closed package, in a dry place protected from light. Exposure to light will cause the silver nitrate tip to turn black, but will not affect the product's potency.

Comment or Questions?

Call (800) 777-4908

Manufacturing Information

Made in England

Manufactured for PSS World Medical, Inc.

4345 Southpoint Blvd.

Jacksonville, FL 32216

Package Label

1655 Each

1655 Case

1655 Box